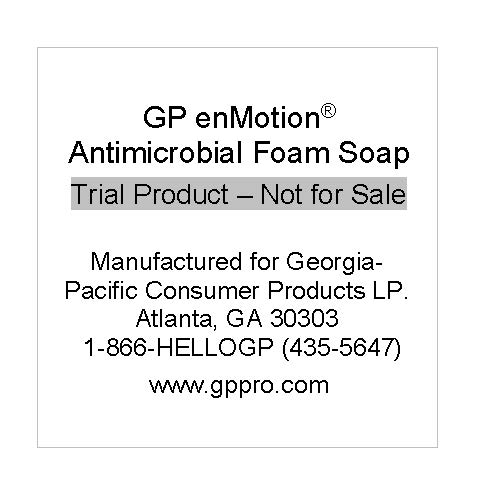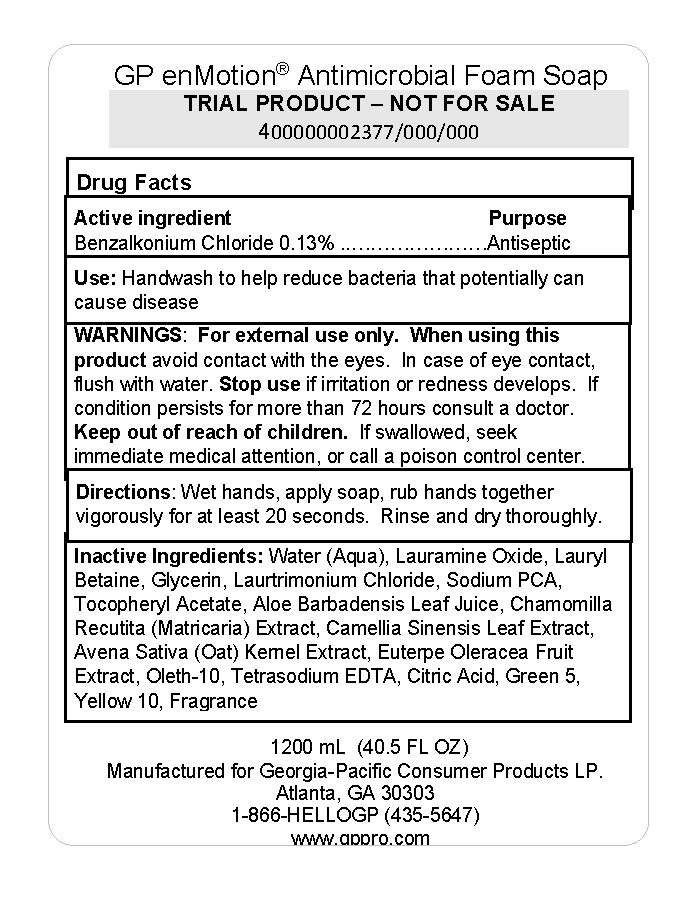 DRUG LABEL: GP enMotion Antimicrobial Foam
NDC: 54622-312 | Form: SOLUTION
Manufacturer: Georgia-Pacific Consumer Products
Category: otc | Type: HUMAN OTC DRUG LABEL
Date: 20240502

ACTIVE INGREDIENTS: BENZALKONIUM CHLORIDE 0.13 g/100 mL
INACTIVE INGREDIENTS: D&C YELLOW NO. 10; .ALPHA.-TOCOPHEROL ACETATE; OAT; LAURTRIMONIUM CHLORIDE; GLYCERIN; SODIUM PYRROLIDONE CARBOXYLATE; ANHYDROUS CITRIC ACID; OLETH-10; WATER; D&C GREEN NO. 5; ALOE VERA LEAF; LAURAMINE OXIDE; EDETATE SODIUM; ACAI; LAURYL BETAINE; GREEN TEA LEAF

54622-312

Drug Facts

Active ingredient

Benzalkonium chloride, 0.13%

Purpose

Antiseptic

Use

Handwash to help reduce bacteria that potentially can cause disease.

Warnings

For external use only

When using this product

Avoid contact with eyes. In case of eye contact, flush with water.

Stop use

if irritation or redness develops. If condition persists for more than 72 hours consult a doctor.

Keep out of reach of children.

If swallowed, seek immediate medical attention or call a poison control center.

Directions

Wet hands, apply soap, rub hands together vigorously for at least 20 seconds.

Rinse and dry hands thoroughly.

Inactive ingredients

Water (Aqua), Lauramine Oxide, Lauryl Betaine, Glycerin, Laurtrimonium Chloride, Sodium PCA, Tocopheryl Acetate, Aloe Barbadensis Leaf Juice, Chamomilla Recutita (Matricaria) Extract, Camellia Sinensis Leaf Extract, Avena Sativa (Oat) Kernel Extract, Euterpe Oleracea Fruit Extract, Oleth-10, Tetrasodium EDTA, Citric Acid, Green 5, Yellow 10, Fragrance